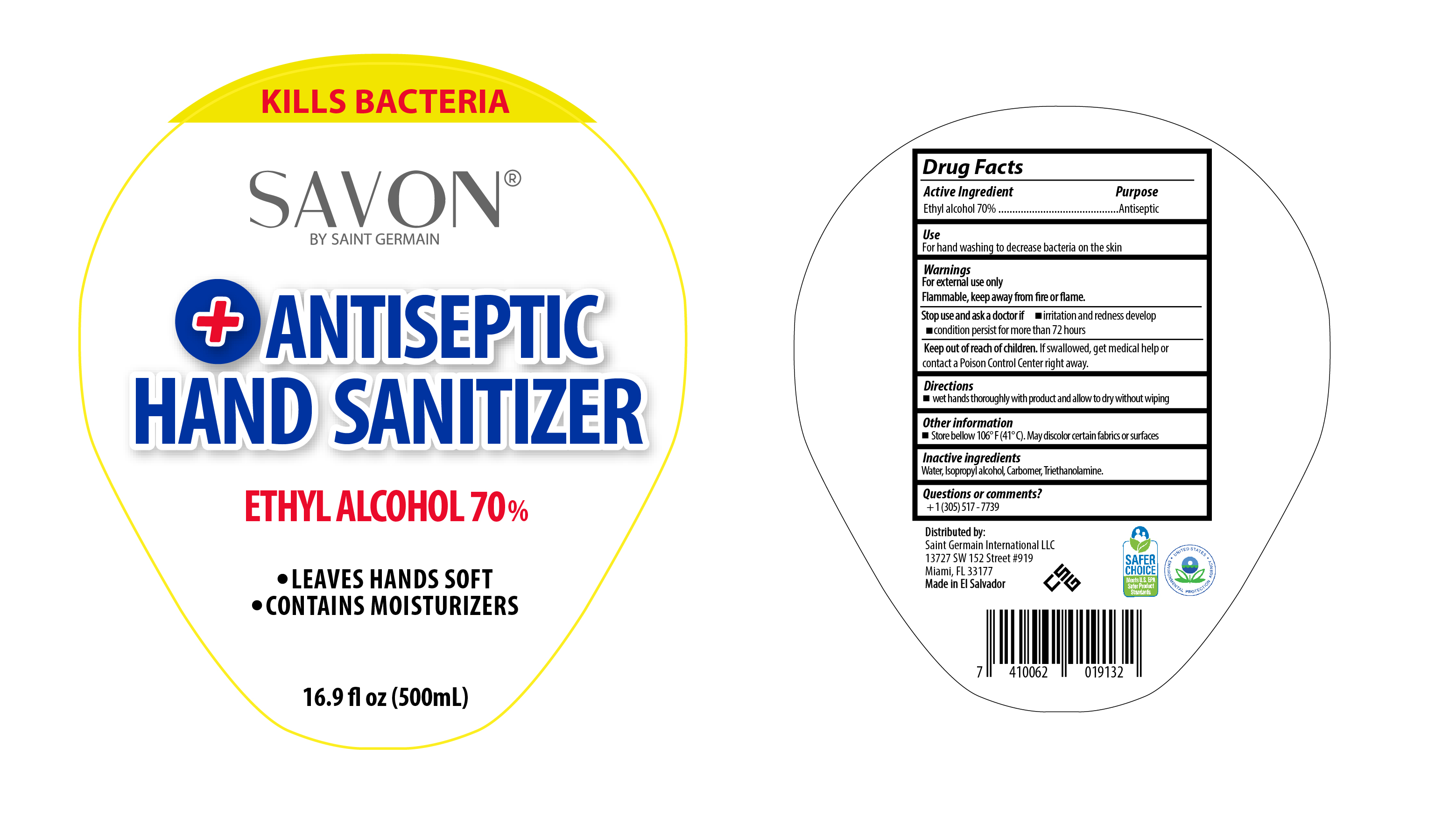 DRUG LABEL: Antiseptic Hand Sanitizer Ethyl Alcohol
NDC: 79036-000 | Form: GEL
Manufacturer: Corporacion Saint Germain
Category: otc | Type: HUMAN OTC DRUG LABEL
Date: 20200805

ACTIVE INGREDIENTS: ALCOHOL 0.7 mL/1 mL
INACTIVE INGREDIENTS: CARBOMER HOMOPOLYMER, UNSPECIFIED TYPE; ISOPROPYL ALCOHOL; TROLAMINE

Antiseptic Alcohol Hand Sanitizer

Active Ingredient

Ethyl Alcohol 70% Purpose:Antiseptic

Purpose

Antiseptic

Uses

- For handwashing to decrease bacteria on the skin.

Warnings

For external use only. Flammable, keep away from fire or flame.

Do not use

- in the eyes

Stop use and ask a doctor if

- irritation and redness develop
- condition persists for more than 72 hours

Keep out of reach of children.

If swallowed, get medical help or contact a Poison Control Center right away.

Directions

- wet hands thoroughly with product and allow to dry without wiping

Other information

- Store below 106ºF (41ºC). May discolor certain fabrics or surfaces.

Inactive ingredients

Water, Isopropyl alcohol, Carbomer, and Triethanolamine.

Questions or comments?

+1 (305)517-7739

Directions

- wet hands thoroughly with product and allow to dry without wiping

PACKAGE LABEL

500 ML NDC:79036-000-02